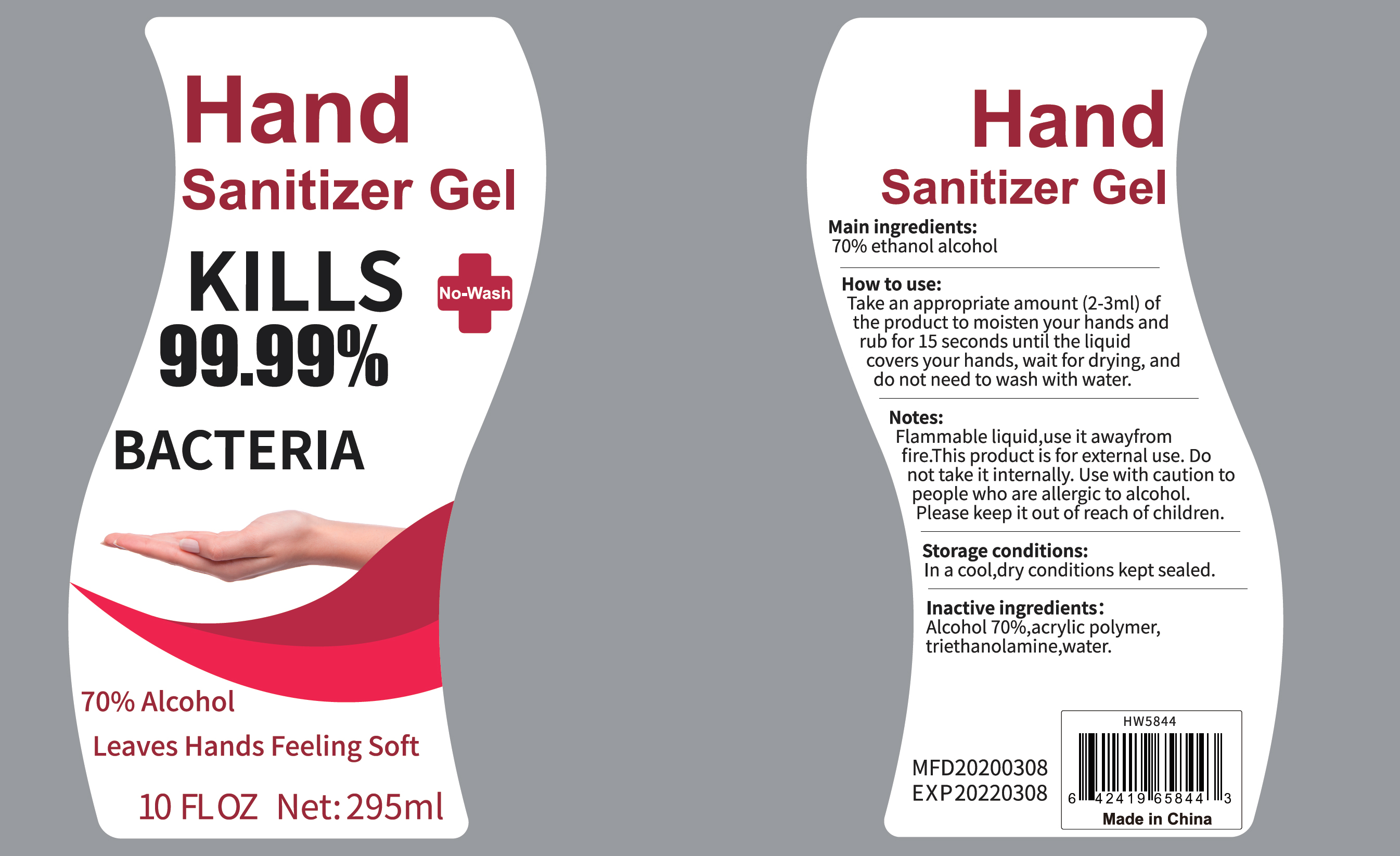 DRUG LABEL: 70% alcohol hand sanitizer (no water)
NDC: 76618-001 | Form: GEL
Manufacturer: Star USA Imports Inc
Category: otc | Type: HUMAN OTC DRUG LABEL
Date: 20230213

ACTIVE INGREDIENTS: ALCOHOL 70 mL/100 mL
INACTIVE INGREDIENTS: CARBOMER 940; WATER; TROLAMINE

70% alcohol hand sanitizer (no water)

Active ingredient

Alcohol 70% v/v. Purpose: Antiseptic

Purpose

Antiseptic. Hand senitizer

INDICATIONS AND USAGE

Hand sanitizer gel, kills 99.99% BACTERIA

Inactive ingredients

Acrylic polymer, triethanolamine, water

Directions

Take an appropriate amount (2-3ml) of the product to moisten your hands and rub for 15 seconds until the liquid covers your hands, wait for drying, and do not need to wash with water

Warnings

Flammable liquid, use it sawy from fire. This product is for external use.

Do not use

Do not take it internally. Use with caution to people who are allergic to alcohol.

Please keep it out of reach of children

STOP USE

Use with caution to people who are allergic to alcohol

WHEN USING

Do not take it internally

Package Label - Principal Display Panel

295 mL NDC: 76618-001-01